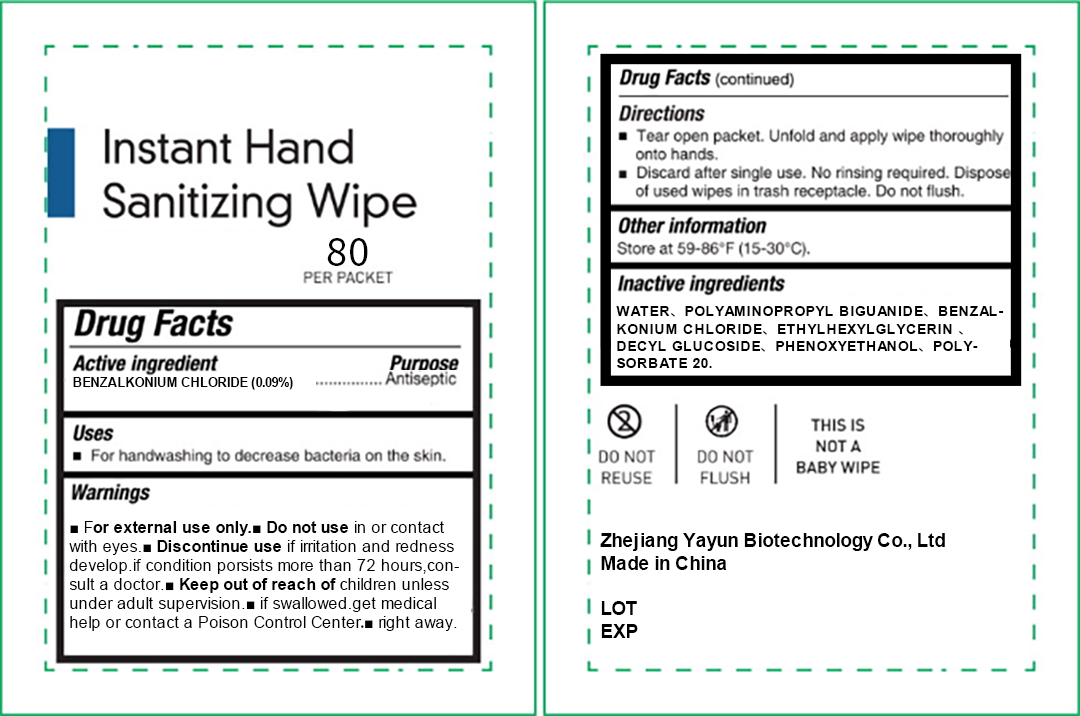 DRUG LABEL: Instant Hand Sanitizeing Wipe
NDC: 96292-001 | Form: CLOTH
Manufacturer: Zhejiang Yayun Biotechnology Co., Ltd.
Category: otc | Type: HUMAN OTC DRUG LABEL
Date: 20201201

ACTIVE INGREDIENTS: BENZALKONIUM CHLORIDE 0.378 g/80 1
INACTIVE INGREDIENTS: ETHYLHEXYLGLYCERIN; WATER; POLYAMINOPROPYL BIGUANIDE; DECYL GLUCOSIDE; PHENOXYETHANOL; POLYSORBATE 20

ACTIVE INGREDIENT

BENZALKONIUM CHLORIDE

PURPOSE

Antiseptic

Uses

For handwashing to decrease bacteria on the skin.

WARNINGS

For external use only.

Do not use in or contactwith eyes.

ASK DOCTOR

Discontinue use if irritation and rednessdevelop.if condition porsists more than 72 hours,consult a doctor.

Keep out of reach of children unless under adult supervision. if swallowed,get medical help or contact a Poison Control Center right away.

Directions

Tear open packet. Unfold and apply wipe thoroughly onto hands.
Discard after single use. No rinsing required. Dispose of used wipes in trash receptacle. Do not flush.

other information

Store at 59-86°F (15-30°C).

INACTIVE INGREDIENT

POLYAMINOPROPYL BIGUANIDE

ETHYLHEXYLGLYCERIN

DECYL GLUCOSIDE

PHENOXYETHANOL

POLYSORBATE 20

WATER